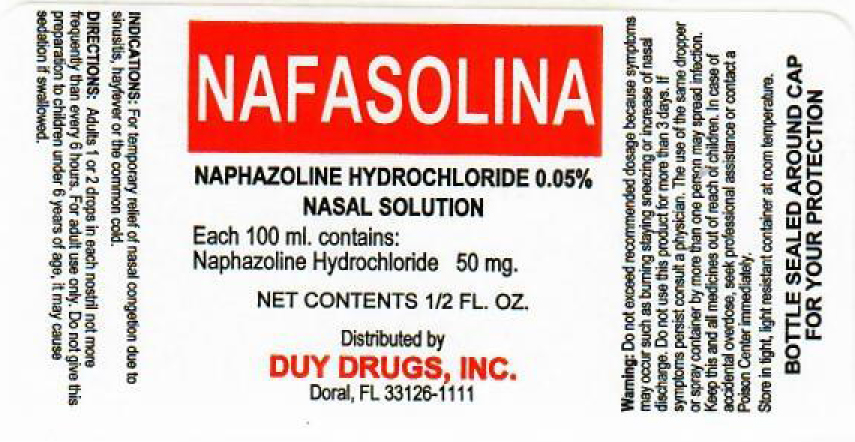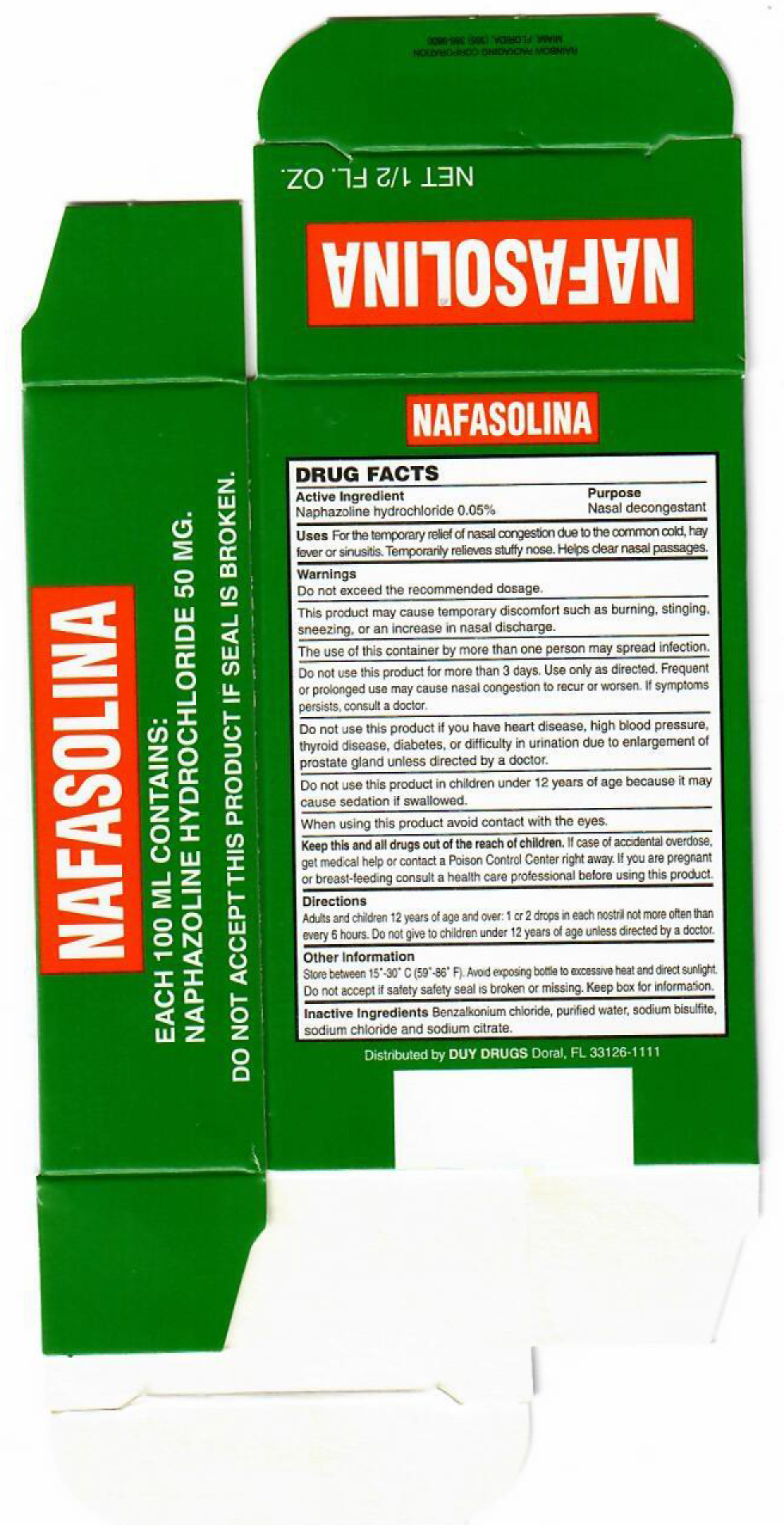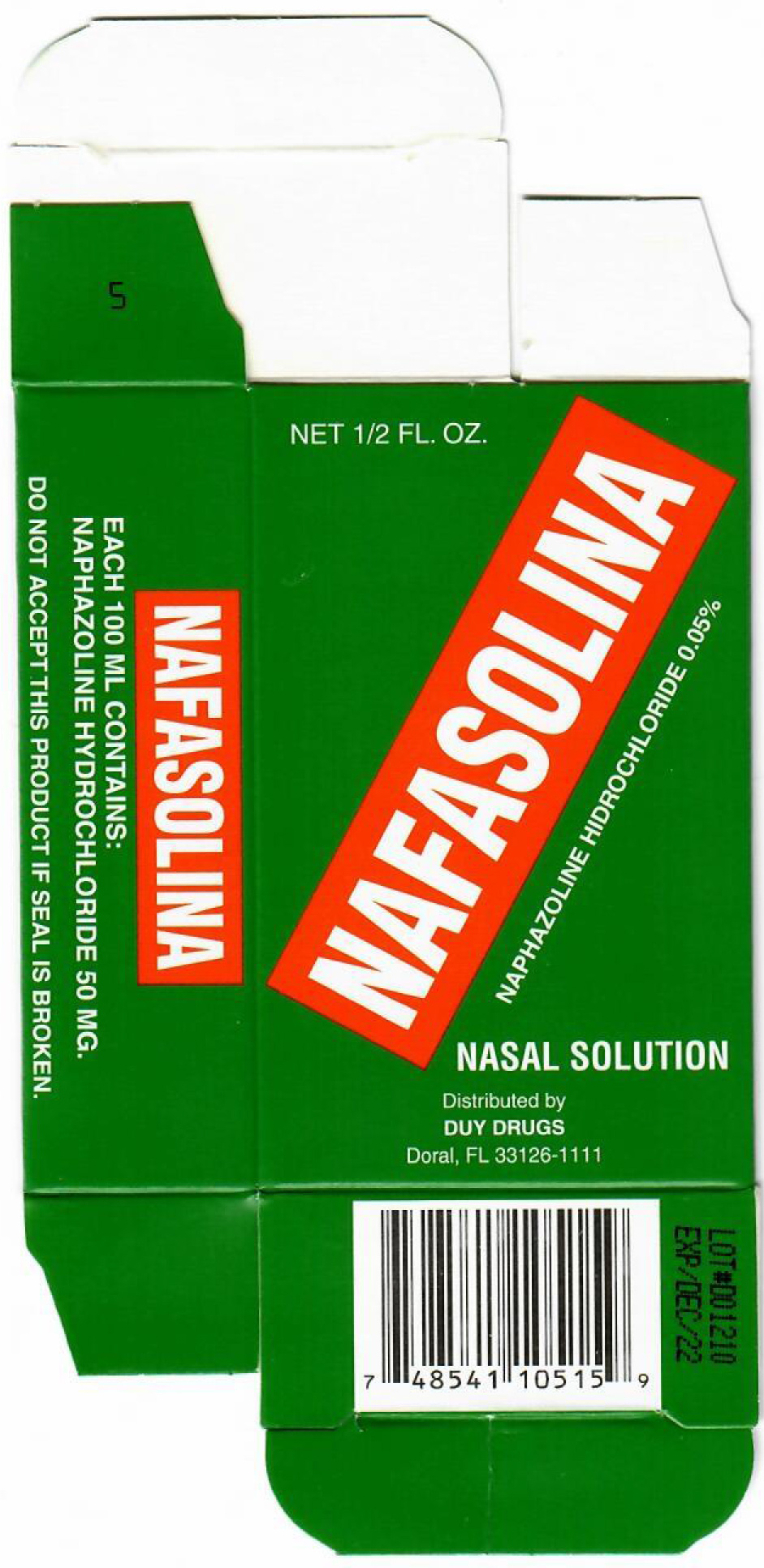 DRUG LABEL: NAFASOLINA
NDC: 48462-001 | Form: SOLUTION/ DROPS
Manufacturer: DUY DRUGS, INC
Category: otc | Type: HUMAN OTC DRUG LABEL
Date: 20210210

ACTIVE INGREDIENTS: NAPHAZOLINE HYDROCHLORIDE 0.376 mg/100 mg
INACTIVE INGREDIENTS: SODIUM CHLORIDE 1 mg/100 mg; BENZALKONIUM CHLORIDE 1 mg/100 mg; SODIUM BISULFITE 1 mg/100 mg; WATER 95.624 mg/100 mg; SODIUM CITRATE 1 mg/100 mg

Naphazoline hydrochloride 0.05% v/v

Active Ingredient(s)

Naphazoline hydrochloride 0.05% v/v. Purpose: Nasal decongestant

Purpose

For the temporary relief of nasal congestion due to the common cold, hay fever, or sinusitis.

Temporarily relieves stuffy nose.

Helps clear nasal passages.

Use

For the temporary relief of nasal congestion due to the common cold, hay fever, or sinusitis.

Warnings

Do not exceed recommended dosage.

This product may cause temporary discomfort such as burning, stinging, sneezing, or an increase in nasal discharge.

The use of this container by more than one person may spread infection.

Do not use this product for more than 3 days. Use only as directed. Frequent or prolonged use may cause nasal congestion to recur or worsen. If symptoms persist, consult a doctor.

Do not use this product if you have heart disease, high blood pressure, thyroid disease, diabetes, or difficulty in urination due to enlargement of the prostate gland unless directed by a doctor.

Do not use this product in children under 12 years of age because it may cause sedation if swallowed.

When using this product avoid contact with the eyes.

Do not use

If you are pregnant or breast-feeding consult a health care professional before using this product.

Do not use this product if you are now taking a prescription monoamine oxidase inhibitor (MAOI) (certain drugs for depression, psychiatric or emotional conditions, or Parkinson's disease), or for 2 weeks after stopping the MAOI drug. If you are uncertain whether your prescription drug contains an MAOI, consult a health professional before taking this product.

Do not use this product for more than 3 days. Use only as directed. Frequent or prolonged use may cause nasal congestion to recur or worsen. If symptoms persist, consult a doctor.

Do not use this product if you have heart disease, high blood pressure, thyroid disease, diabetes, or difficulty in urination due to enlargement of the prostate gland unless directed by a doctor.

Do not use this product in children under 12 years of age because it may cause sedation if swallowed.

Do not use this product in a child who has heart disease, high blood pressure, thyroid disease, or diabetes unless directed by a doctor.

WHEN USING

This product is for nasal use only.

When using this product avoid contact with the eyes. In case of contact with eyes, rinse eyes thoroughly with water.

Keep out of reach of children. In case of accidental overdose, get medical help or contact a Poison Control Center right away.

Stop using this product after 3 days.

If symptoms persist, stop, and consult a doctor.

Keep out of reach of children.

In case of accidental overdose, get medical help or contact a Poison Control Center right away.

If you are pregnant or breast-feeding consult a health care professional before using this product.

Directions

Adults and children 12 years of age and over: 1 or 2 drops in each nostril not more often than every 6 hours. Do not give to children under 12 years of age unless directed by a doctor.

Other information

Store between 15°-30°C (59°-86°F).

Avoid exposing bottle to excessive heat and direct sunlight.

Do not accept this product if safety seal is broken or missing.

Keep box for information.

Inactive ingredients

Benzalkonium chloride, purified water, sodium bisulfite, sodium chloride, and sodium citrate.

Package Label - Principal Display Panel

0.5 FL. OZ NDC: 48462-001-01

Drug Facts Panel on Outer Box

0.5 FL. OZ NDC: 48462-001-02

Name of Product Outer box

0.5 FL. OZ NDC: 48462-001-02